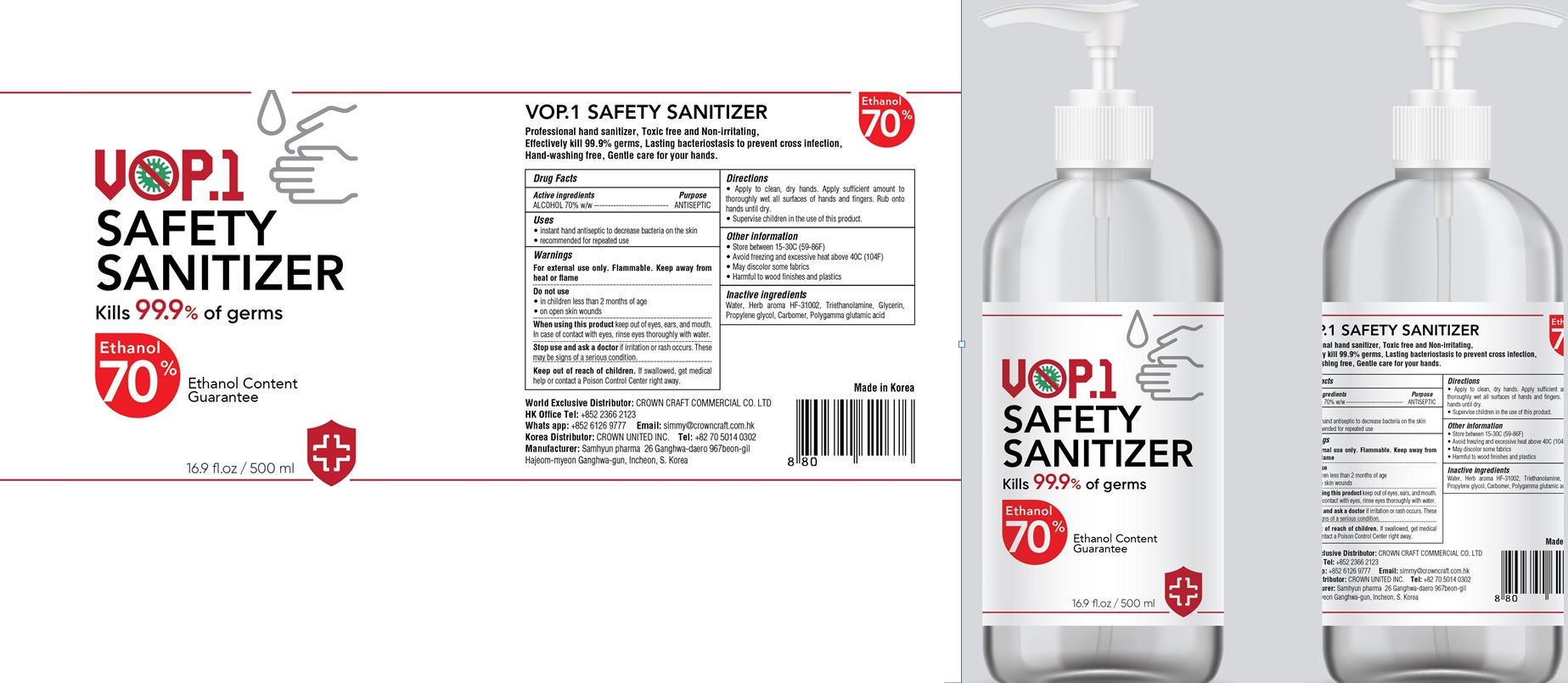 DRUG LABEL: VOP.1 Safety Sanitizer
NDC: 77815-010 | Form: GEL
Manufacturer: Crown United
Category: otc | Type: HUMAN OTC DRUG LABEL
Date: 20200527

ACTIVE INGREDIENTS: ALCOHOL 350 g/500 mL
INACTIVE INGREDIENTS: Water; TROLAMINE; Glycerin; Propylene glycol; CARBOMER HOMOPOLYMER, UNSPECIFIED TYPE

ACTIVE INGREDIENT

ALCOHOL 70% w/w

INACTIVE INGREDIENTS

Water, Herb aroma HF-31002, Triethanolamine, Glycerin, Propylene glycol, Carbomer, Polygamma glutamic acid

Purpose

ANTISEPTIC

Warnings

For external use only. Flammable. Keep away from heat or flame
--------------------------------------------------------------------------------------------------------
Do not use
• in children less than 2 months of age
• on open skin wounds
--------------------------------------------------------------------------------------------------------
When using this product keep out of eyes, ears, and mouth. In case of contact with eyes, rinse eyes thoroughly with water.
--------------------------------------------------------------------------------------------------------
Stop use and ask a doctor if irritation or rash occurs. These may be signs of a serious condition.

KEEP OUT OF REACH OF CHILDREN

If swallowed, get medical help or contact a Poison Control Center right away.

Uses

•instant hand antiseptic to decrease bacteria on the skin
•recommended for repeated use

Directions

• Apply to clean, dry hands. Apply sufficient amount to thoroughly wet all surfaces of hands and fingers. Rub onto hands until dry.
• Supervise children in the use of this product.

Other information

• Store between 15-30C (59-86F)
• Avoid freezing and excessive heat above 40C (104F)
• May discolor some fabrics
• Harmful to wood finishes and plastics